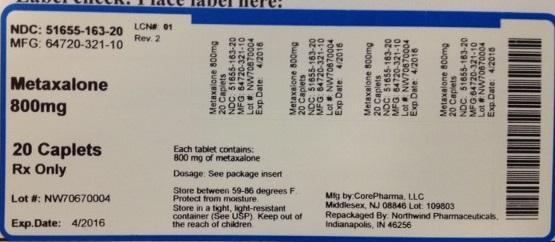 DRUG LABEL: Metaxalone
NDC: 51655-163 | Form: TABLET
Manufacturer: Northwind Pharmaceuticals
Category: prescription | Type: HUMAN PRESCRIPTION DRUG LABEL
Date: 20140603

ACTIVE INGREDIENTS: METAXALONE 800 mg/1 1

PACKAGE LABEL

NDC: 51655-163-20

MFG: 64720-321-10

Metaxalone 800mg

20 caplets

Rx only

Lot#:

Exp. date:

Each tablet contains 800 mg of metaxalone

Dosage: See package insert

Store between 59-86 degrees F.

Protect from moisture.

Store in a tight, light-resistant container (See USP).

Keep out of the reach of children.

Mfg. by: CorePharma, LLC Middlesex, NJ 08846

Repackaged by: Northwind Pharmaceuticals, Indianapolis, IN 46256